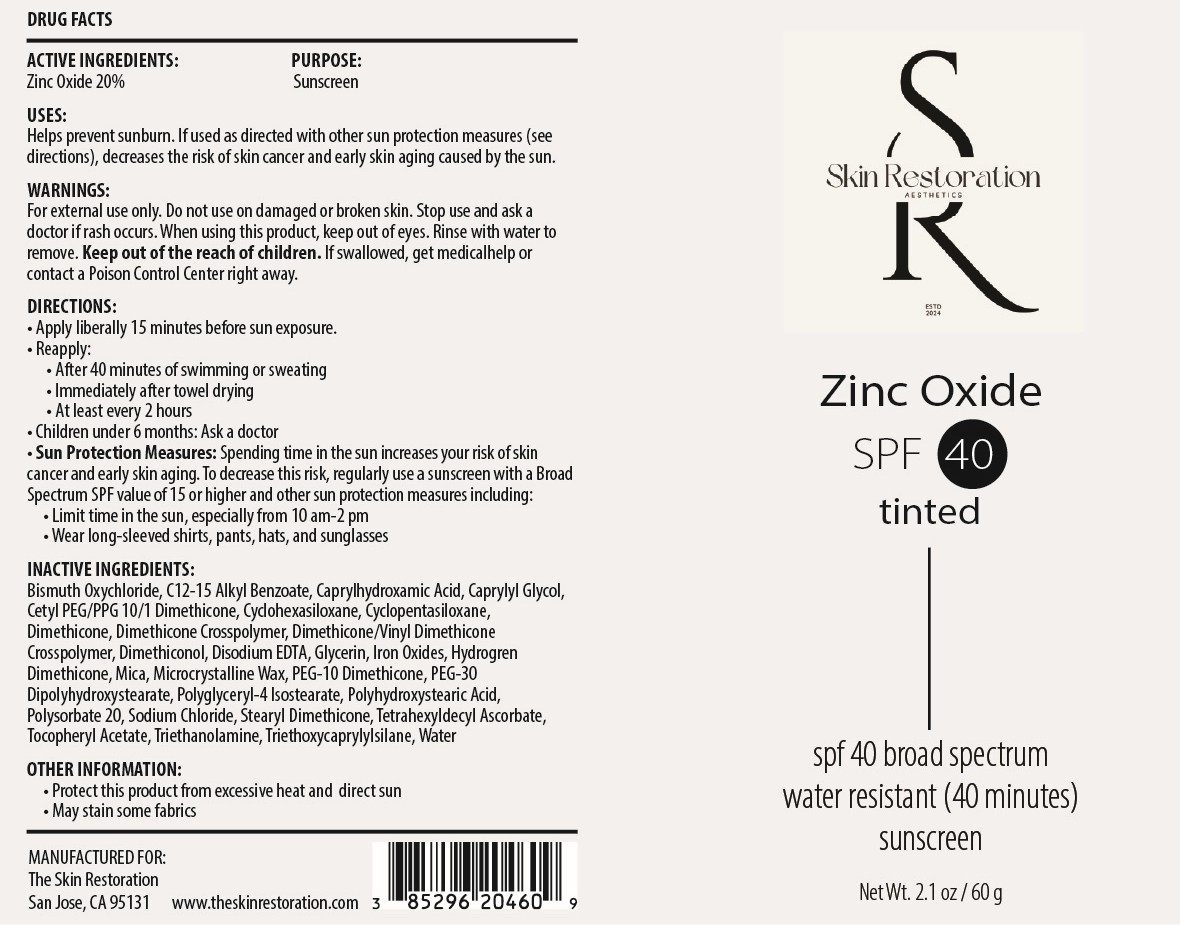 DRUG LABEL: Zinc Oxide SPF 40 Tinted
NDC: 85296-204 | Form: CREAM
Manufacturer: Skin Restoration Aesthetics
Category: otc | Type: HUMAN OTC DRUG LABEL
Date: 20251208

ACTIVE INGREDIENTS: ZINC OXIDE 200 mg/1 g
INACTIVE INGREDIENTS: CI 77492; MICROCRYSTALLINE WAX; POLYHYDROXYSTEARIC ACID (2300 MW); POLYSORBATE 20; ALPHA-TOCOPHEROL ACETATE; TRIETHOXYCAPRYLYLSILANE; DIMETHICONE; CI 77491; TETRAHEXYLDECYL ASCORBATE; BISMUTH OXYCHLORIDE; EDETATE DISODIUM ANHYDROUS; WATER; DIMETHICONE CROSSPOLYMER; CETYL PEG/PPG-10/1 DIMETHICONE (HLB 4); CYCLOPENTASILOXANE; POLYGLYCERYL-4 ISOSTEARATE; SODIUM CHLORIDE; STEARYL DIMETHICONE (400 MPA.S AT 50C); TRIETHANOLAMINE; C12-15 ALKYL BENZOATE; CAPRYLYL GLYCOL; DIMETHICONE/VINYL DIMETHICONE CROSSPOLYMER (SOFT PARTICLE); HYDROGEN DIMETHICONE (20 CST); PEG-10 DIMETHICONE (600 CST); GLYCERIN; CYCLOHEXASILOXANE; MICA; CAPRYLHYDROXAMIC ACID; DIMETHICONOL (2000 CST); PEG-30 DIPOLYHYDROXYSTEARATE; CI 77499

Active Ingredient:

Zinc Oxide 20%

Purpose:

Sunscreen

Uses:

Helps prevents sunburn. If used as directed with other sun protection measures (see Directions), decreases the risk of skin cancer and early skin aging caused by the sun.

Warnings:

For external use only. Do not use on damaged or broken skin. Stop use and ask a doctor if rash occurs. When using this product, keep out of eyes. Rinse with water to remove. Keep out of the reach of children. If swallowed, get medicalhelp or contact a Poison Control Center right away.

Directions:

• Apply liberally 15 minutes before sun exposure. • Reapply: • After 40 minutes of swimming or sweating • Immediately after towel drying • At least every 2 hours • Children under 6 months: Ask a doctor • Sun Protection Measures: Spending time in the sun increases your risk of skin cancer and early skin aging. To decrease this risk, regularly use a sunscreen with a Broad Spectrum SPF value of 15 or higher and other sun protection measures including: • Limit time in the sun, especially from 10 am-2 pm • Wear long-sleeved shirts, pants, hats, and sunglasses

Inactive Ingredients:

Bismuth Oxychloride, C12-15 Alkyl Benzoate, Caprylhydroxamic Acid, Caprylyl Glycol, Cetyl PEG/PPG-10/1 Dimethicone, Cyclohexasiloxane, Cyclopentasiloxane, Dimethicone, Dimethicone Crosspolymer, Dimethicone/Vinyl Dimethicone Crosspolymer, Dimethiconol, Disodium EDTA, Glycerin, Hydrogen Dimethicone, Iron Oxides, Mica, Microcrystalline Wax, PEG-10 Dimethicone, PEG-30 Dipolyhydroxystearate, Polyglyceryl-4 Isostearate, Polyhydroxystearic Acid, Polysorbate 20, Sodium Chloride, Stearyl Dimethicone, Tetrahexyldecyl Ascorbate, Tocopheryl Acetate, Triethanolamine, Triethoxycaprylylsilane, Water

Other Information:

• Protect this product from excessive heat and direct sun • May stain some fabrics

Warning:

Keep out of the reach of children